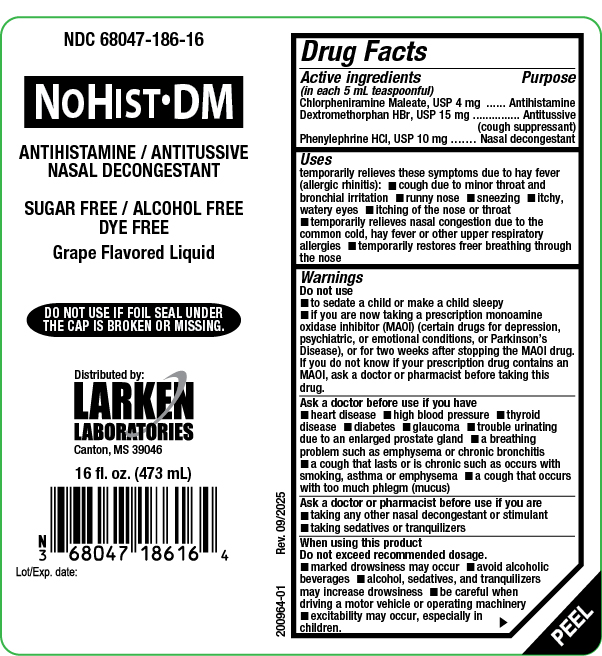 DRUG LABEL: NoHist DM
NDC: 68047-186 | Form: LIQUID
Manufacturer: Larken Laboratories, Inc.
Category: otc | Type: HUMAN OTC DRUG LABEL
Date: 20251016

ACTIVE INGREDIENTS: CHLORPHENIRAMINE MALEATE 4 mg/5 mL; PHENYLEPHRINE HYDROCHLORIDE 10 mg/5 mL; DEXTROMETHORPHAN HYDROBROMIDE 15 mg/5 mL
INACTIVE INGREDIENTS: GLYCERIN; METHYLPARABEN; PROPYLENE GLYCOL; PROPYLPARABEN; ANHYDROUS CITRIC ACID; EDETATE DISODIUM; WATER; SACCHARIN SODIUM; TRISODIUM CITRATE DIHYDRATE

NoHist DM

Drug Facts

Active Ingredients

(In each 5 mL teaspoonful)

Chlorpheniramine Maleate, USP 4 mg

Dextromethorphan HBr, USP 15 mg

Phenylephrine HCl, USP 10 mg

Purpose

Chlorpheniramine Maleate Antihistamine

Dextromethorphan HBr Antitussive (cough suppressant)

Phenylephrine HCl Nasal decongestant

Uses

temporarily relieves these symptoms due to hay fever (allergic rhinitis):

- cough due to minor throat and bronchial irritation
- runny nose
- sneezing
- itchy, watery eyes
- itching of the nose or throat
- temporarily relieves nasal congestion due to the common cold, hay fever or other upper respiratory allergies
- temporarily restores freer breathing through the nose

Warnings

Do not use

- to sedate a child or make a child sleepy
- if you are now taking a prescription monoamine oxidase inhibitor (MAOI) (certain drugs for depression, psychiatric, or emotional conditions, or Parkinson's disease), or for two weeks after stopping the MAOI drug. If you do not know if your prescription drug contains an MAOI, ask a doctor or pharmacist before taking this drug.

Ask a doctor before use if you have

- heart disease
- high blood pressure
- thyroid disease
- diabetes
- glaucoma
- trouble urinating due to an enlarged prostate gland
- a breathing problem such as emphysema or chronic bronchitis
- a cough that lasts or is chronic such as occurs with smoking, asthma or emphysema
- a cough that occurs with too much phlegm (mucus)

Ask a doctor or pharmacist before use if you are

- taking any other nasal decongestant or stimulant
- taking sedatives or tranquilizers

When using this product

Do not exceed recommended dosage.

- marked drowsiness may occur
- avoid alcoholic beverages
- alcohol, sedatives, and tranquilizers may increase drowsiness
- be careful when driving a motor vehicle or operating machinery
- excitability may occur, especially in children

Stop use and ask a doctor if

- nervousness, dizziness, or sleeplessness occur.
- cough or nasal congestion persists for more than 1 week, tends to recur, or is accompanied by a fever, rash or persistent headache. These could be signs of a serious condition.

If pregnant or breast-feeding

ask a health professional before use.

Keep out of the reach of children

In case of overdose, get medical help or contact a Poison Control Center immediately.

Directions

Do not exceed 6 doses in a 24-hour period

Age | Dose
Adults and children over 12 years of age | 1 teaspoonsful (5 mL) every 4 hours
Children 6 to under 12 years of age | 1/2 teaspoonsful (2.5 mL) every 4 hours
Children under 6 years of age | Ask your doctor

Other Information

- store at 20°-25°C (68°-77°F)
- very low sodium, contains 5 mg sodium per 5 mL teaspoonful

Inactive Ingredients

citric acid, edetate disodium, glycerin, grape flavoring, methylparaben, propylene glycol, propylparaben, purified water, saccharin sodium, and sodium citrate dihydrate

Questions or Comments

Call 1-601-855-7678 weekdays from 9:00 am to 4:00 pm CST or go to http://www.larkenlabs.com.

Principal Display Panel

Figure 1:16 oz. Bottle Label